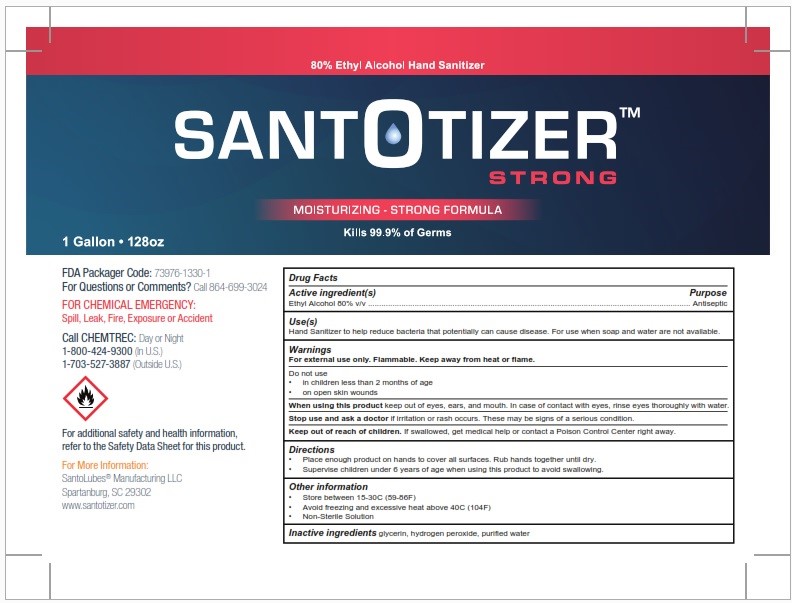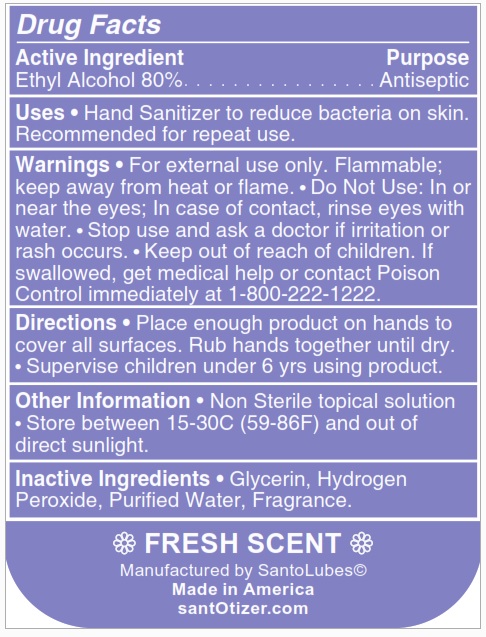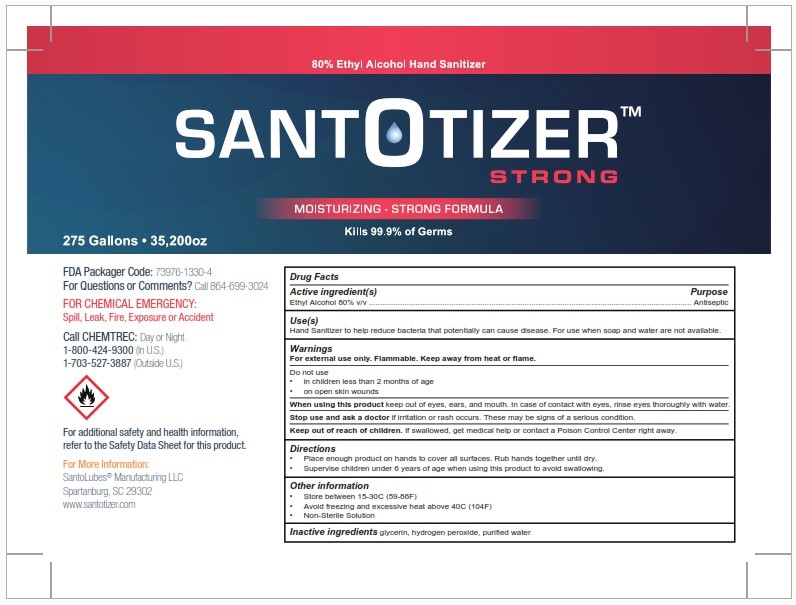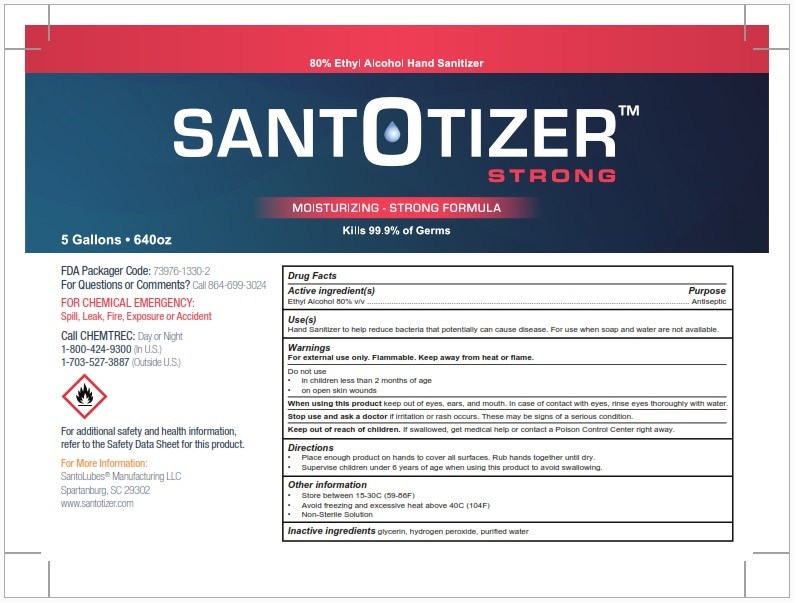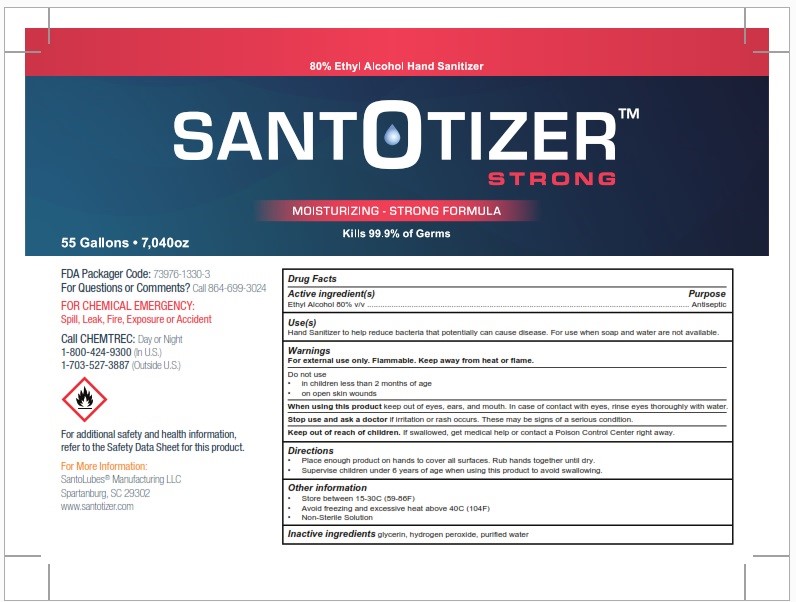 DRUG LABEL: SantOtizer E80- FRAGRANCE
NDC: 73976-3304 | Form: LIQUID
Manufacturer: SantoLubes LLC
Category: otc | Type: HUMAN OTC DRUG LABEL
Date: 20210429

ACTIVE INGREDIENTS: ALCOHOL 80 mL/100 mL
INACTIVE INGREDIENTS: WATER 18.3 mL/100 mL; GLYCERIN 1.45 mL/100 mL; HYDROGEN PEROXIDE 0.125 mL/100 mL

ACTIVE INGREDIENT

Alcohol 80% v/v

Purpose

Antiseptic

INDICATIONS AND USAGE

Use[s]

Hand Sanitizer to help reduce bacteria that potentially can cause disease. For use when soap and water are not available.

Warnings

For external use only. Flammable. Keep away from heat or flame.

Do not use

In children less than 2 months of age
On open skin wounds

When using this product keep out of eyes, ears, and mouth. In case of contact with eyes, rinse eyes thoroughly with water.

Stop use and ask a doctor if irritation or rash occurs. These may be signs of a serious condition.

Keep out of reach of children. If swallowed, get medical help or contact a Poison Control Center right away.

Directions

Place enough product on hands to cover all surfaces. Rub hands together until dry.

Supervise children under 6 years of age when using this product to avoid swallowing.

Other information

Store between 15-30C (59-86F)
Avoid freezing and excessive heat above 40C (104F)

INACTIVE INGREDIENT

fragrance, glycerin, hydrogen peroxide, purified water

PACKAGE LABEL

3,600ml NDC 73976-3304-1

18,000ml NDC 73976-3304-2

200,000ml NDC 73976-3304-3

1,022,00ml NDC 73976-3304-4